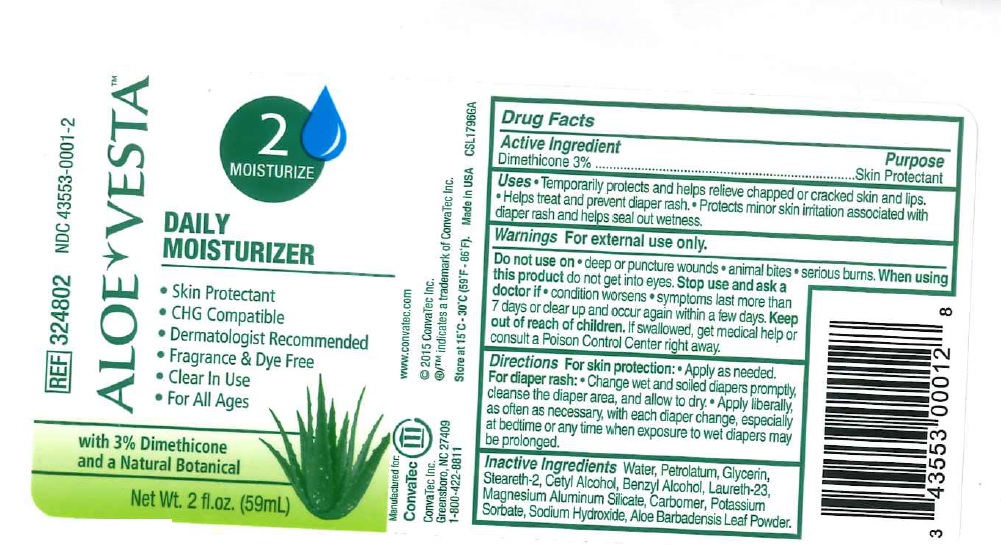 DRUG LABEL: Aloe Vesta Daily Moisturizer 59 ml
NDC: 11099-0001 | Form: LOTION
Manufacturer: Guest Packaging LLC.
Category: otc | Type: HUMAN OTC DRUG LABEL
Date: 20160806

ACTIVE INGREDIENTS: DIMETHICONE 1.77 g/59 mL
INACTIVE INGREDIENTS: WATER; PETROLATUM; GLYCERIN; STEARETH-2; CETYL ALCOHOL; BENZYL ALCOHOL; LAURETH-23; MAGNESIUM ALUMINUM SILICATE; CARBOMER HOMOPOLYMER TYPE B (ALLYL SUCROSE CROSSLINKED); POTASSIUM SORBATE; SODIUM HYDROXIDE; ALOE VERA LEAF

Aloe VestaTM Daily Moisturizer 59ml

INDICATIONS AND USAGE

Uses • Temporarily protects and helps relieve chapped or cracked skin and lips.• Helps treat and prevent diaper rash. • Protects minor skin irritation associated with diaper rash and helps seal out wetness.

Warnings For external use only.
Do not use on • deep or puncture wounds • animal bites • serious burns. When using this product do not get into eyes.
Stop use and ask a doctor if • condition worsens • symptoms last more than 7 days or clear up and occur again within a few days.

Keep out of reach of children. If swallowed, get medical help or consult a Poison Control Center right away.

DOSAGE AND ADMINISTRATION

Directions For skin protection: •Apply as needed.
For diaper rash: • Change wet and soiled diapers promptly, cleanse the diaper area, and allow to dry.
• Apply liberally, as often as necessary, with each diaper change, especially at bedtime or any time when exposure to wet diapers may be prolonged.

Active ingredient

Dimethicone 3%

Purpose

Skin Protectant

INACTIVE INGREDIENT

Inactive ingredients: Water, Petrolatum, Glycerin, Steareth-2, Cetyl Alcohol, Benzyl Alcohol, Laureth-23, Magnesium Aluminum Silicate, Carbomer, Potassium Sorbate, Sodium Hydroxide, Aloe Barbadensis Leaf juice.

STORAGE AND HANDLING

Store at 15°C to 30°C (59°F - 86°F)

- Skin Protectant
- CHG Compatible
- Dermatologist Recommended
- Fragrance & Dye Free
- Clear In Use
- For All Ages

with 3 percent Dimethicone and a Natural Botanical

Manufactured for:
ConvaTec
ConvaTec Inc.
Greensboro, NC 27409
1-800-422-8811
www.convatec.com

Made in USA